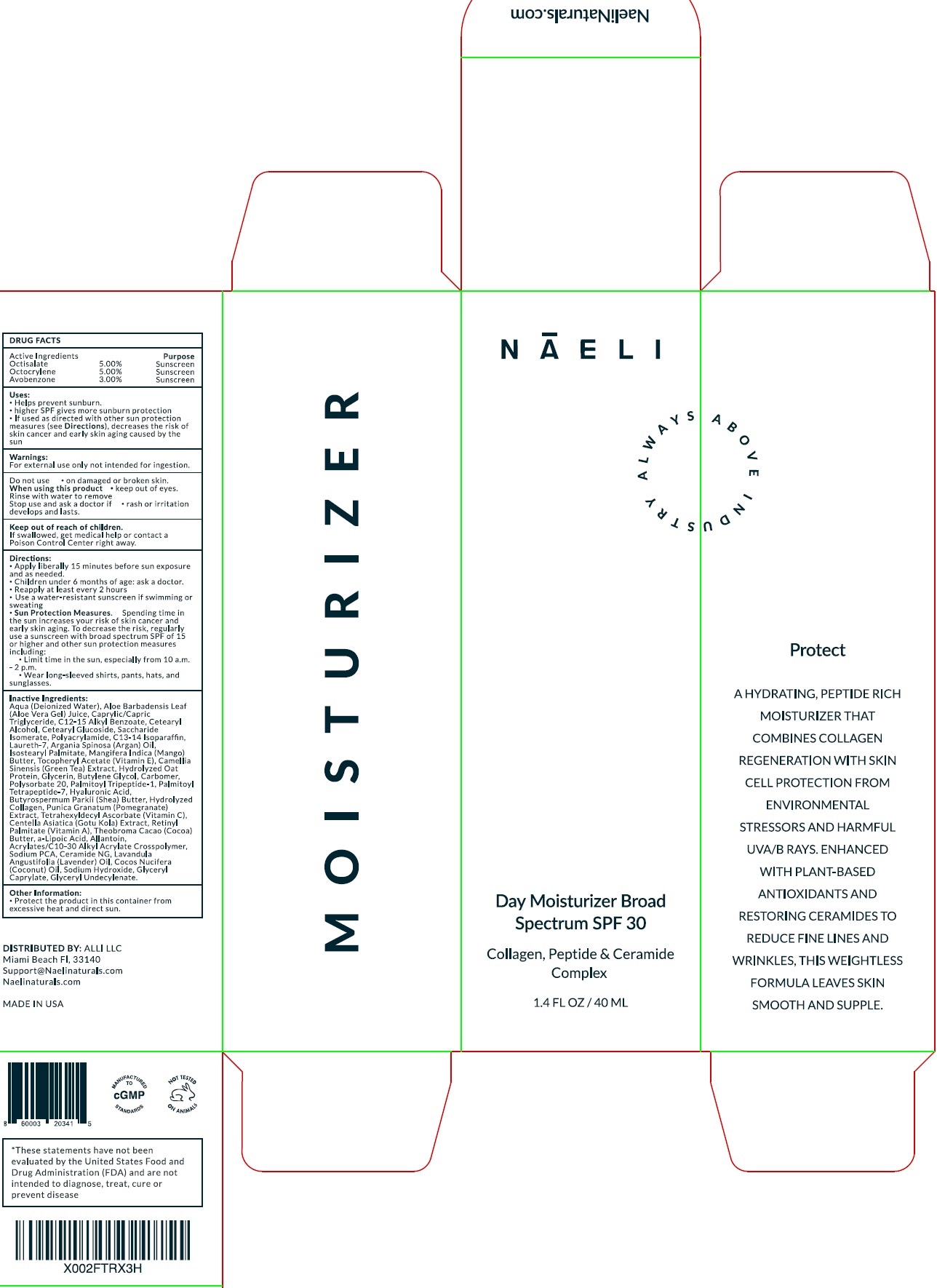 DRUG LABEL: NAELI Day Moisturizer SPF 30
NDC: 73670-049 | Form: LOTION
Manufacturer: Alli LLC
Category: otc | Type: HUMAN OTC DRUG LABEL
Date: 20231105

ACTIVE INGREDIENTS: OCTISALATE 50 mg/1 mL; OCTOCRYLENE 50 mg/1 mL; AVOBENZONE 30 mg/1 mL
INACTIVE INGREDIENTS: WATER; ALOE VERA LEAF; MEDIUM-CHAIN TRIGLYCERIDES; ALKYL (C12-15) BENZOATE; CETOSTEARYL ALCOHOL; CETEARYL GLUCOSIDE; SACCHARIDE ISOMERATE; C13-14 ISOPARAFFIN; LAURETH-7; ARGAN OIL; ISOSTEARYL PALMITATE; MANGO; .ALPHA.-TOCOPHEROL ACETATE; GREEN TEA LEAF; GLYCERIN; BUTYLENE GLYCOL; CARBOMER HOMOPOLYMER, UNSPECIFIED TYPE; POLYSORBATE 20; PALMITOYL TRIPEPTIDE-1; PALMITOYL TETRAPEPTIDE-7; HYALURONIC ACID; SHEA BUTTER; POMEGRANATE; TETRAHEXYLDECYL ASCORBATE; CENTELLA ASIATICA WHOLE; VITAMIN A PALMITATE; COCOA; ALLANTOIN; CARBOMER INTERPOLYMER TYPE A (ALLYL SUCROSE CROSSLINKED); SODIUM PYRROLIDONE CARBOXYLATE; CERAMIDE NG; LAVENDER OIL; COCONUT OIL; SODIUM HYDROXIDE; GLYCERYL MONOCAPRYLATE; GLYCERYL 1-UNDECYLENATE

NAELI Day Moisturizer SPF 30

Active Ingredients

Octisalate 5.00%

Octocrylene 5.00%

Avobenzone 3.00%

Purpose

Sunscreen

Uses:

- Helps prevent sunburn.
- higher SPF gives more sunburn protection
- If used as directed with other sun protection measures (see), decreases the risk of skin cancer and early skin aging caused by the sun Directions

Warnings:

For external use only not intended for ingestion.

Do not use

on damaged or broken skin.

When using this product

keep out of eyes. Rinse with water to remove

Stop use and ask a doctor if

rash or irritation develops and lasts.

Keep out of reach of children.

If swallowed, get medical help or contact a Poison Control Center right away.

Directions:

- Apply liberally 15 minutes before sun exposure and as needed.
- Children under 6 months of age: ask a doctor.
- Reapply at least every 2 hours
- Use a water-resistant sunscreen if swimming or sweating
- Spending time in the sun increases your risk of skin cancer and early skin aging. To decrease the risk, regularly use a sunscreen with broad spectrum SPF of 15 or higher and other sun protection measures including: Sun Protection Measures.
- Limit time in the sun, especially from 10 a.m.-2 p.m.
- Wear long-sleeved shirts, pants, hats, and sunglasses.

Inactive Ingredients:

Aqua (Deionized Water), Aloe Barbadensis Leaf (Aloe Vera Gel) Juice, Caprylic/Capric Triglyceride, C12-15 Alkyl Benzoate, Cetearyl Alcohol, Cetearyl Glucoside, Saccharide Isomerate, Polyacrylamide, C13-14 Isoparaffin, Laureth-7, Argania Spinosa (Argan) Oil, Isostearyl Palmitate, Mangifera Indica (Mango) Butter, Tocopheryl Acetate (Vitamin E), Camellia Sinensis (Green Tea) Extract, Hydrolyzed Oat Protein, Glycerin, Butylene Glycol, Carbomer, Polysorbate 20, Palmitoyl Tripeptide-1, Palmitoyl Tetrapeptide-7, Hyaluronic Acid, Butyrospermum Parkii (Shea) Butter, Hydrolyzed Collagen, Punica Granatum (Pomegranate) Extract, Tetrahexyldecyl Ascorbate (Vitamin C), Centella Asiatica (Gotu Kola) Extract, Retinyl Palmitate (Vitamin A), Theobroma Cacao (Cocoa) Butter, a-Lipoic Acid, Allantoin, Acrylates/C10-30 Alkyl Acrylate Crosspolymer, Sodium PCA, Ceramide NG, Lavandula Angustifolia (Lavender) Oil, Cocos Nucifera (Coconut) Oil, Sodium Hydroxide, Glyceryl Caprylate, Glyceryl Undecylenate.

Other Information:

- Protect the product in this container from excessive heat and direct sun.